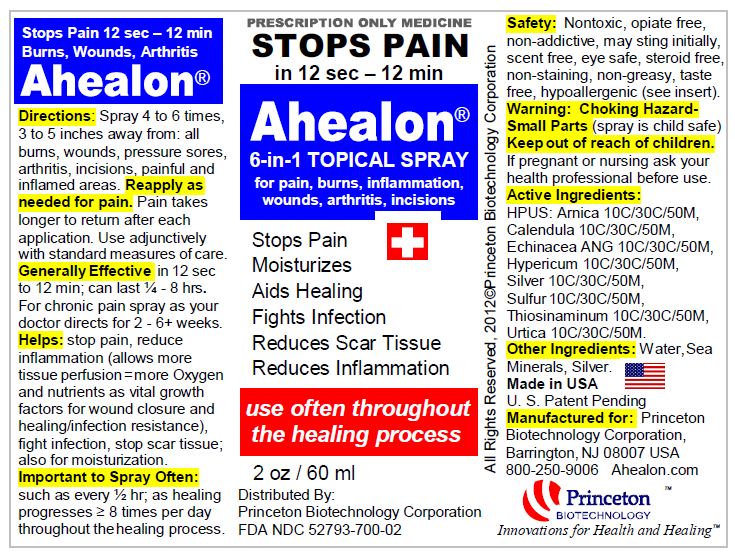 DRUG LABEL: Ahealon 
NDC: 52793-700 | Form: SPRAY
Manufacturer: PRINCETON BIOTECHNOLOGY CORPORATION
Category: homeopathic | Type: HUMAN PRESCRIPTION DRUG LABEL
Date: 20200130

ACTIVE INGREDIENTS: Arnica Montana 30 [kp_C]/60 mL; Calendula Officinalis Flowering Top 30 [kp_C]/60 mL; Echinacea Angustifolia 30 [kp_C]/60 mL; St. John's Wort 30 [kp_C]/60 mL; Silver 30 [kp_C]/60 mL; Sulfur 30 [kp_C]/60 mL; Allylthiourea 30 [kp_C]/60 mL; Urtica Urens 30 [kp_C]/60 mL
INACTIVE INGREDIENTS: Water

AHEALON®

CAUTION:

Federal law prohibits dispensing without a prescription.

DESCRIPTION:

AHEALON® is a US Patent Pending biochemical homeopathic medication indicated for the treatment of pain and or inflammation, as well as a general healing aid, an infection deterrent, an agent to help reduce scar tissue and a source of moisturization (dry/cracked/burned skin); treatment can include: burn injuries, radiation dermatitis, arthritis (including osteoarthritis, rheumatoid arthritis, and psoriatic arthritis), rashes, wounds (chronic/acute), pressure sores, neuropathic discomfort and any generally inflamed area. The active ingredients in AHEALON consist of the following: Arnica 10C/30C/50M, Calendula 10C/30C/50M, Echinacea ANG 10C/30C/50M, Hypericum 10C/30C/50M, Silver 10C/30C/50M, Sulfur 10C/30C/50M, Thiosinaminum 10C/30C/50M, Urtica 10C/30C/50M. These drug ingredients are listed in the Homoeopathic Pharmacopoeia of the United States (HPUS).[1]

Inactive ingredients: Sea Minerals, Silver, Water.

Pharmacological Class: Homeopathic drug.

Dosage form: Liquid; may be used topically at 0.15 ML per spray application. Liquid; may be used as a gauze saturant. Liquid; may be aerosolized for bronchial/sinus use.

CLINICAL PHARMACOLOGY:

The active ingredients in AHEALON are simple biochemical compounds. The exact mechanism of action is unknown, however it is believed that AHEALON helps to stimulate healing response mechanisms.

ARNICA has been used for medicinal purposes since the 1500s. In general the constituent base is complex, consisting of a wide variety of chemicals of variable effect and potency; for example, one such complex can contain derivatives of thymol[2] also known as 2-isopropyl-5-methylphenol, a naturally occurring biocide with strong antimicrobial/anti-fungal attributes[3] that can reduce bacterial resistance to common drugs such as penicillin.[4] Numerous studies have demonstrated its antimicrobial (including Aeromoans hydrophila and Staphylococcus aureus)[5] effects, ranging from inducing antibiotic susceptibility in drug-resistant pathogens to powerful antioxidant properties,[6] and to reduce bacterial resistance to antibiotics through a synergistic effect;[7] it has also been shown to be effective particularly against Fluconazole-resistant strains, and there is evidence of anti-tumor properties.[8] Today Arnica is generally used to reduce inflammation, and to heal wounds. It is also commonly used for injuries such as sprains and bruises.[9] Some surgeons recommend Arnica to speed recovery from soreness and bruising associated with surgery.

CALENDULA plant pharmacological studies have suggested that Calendula extracts may have anti-viral, antigenotoxic, cytotoxic anti-tumor, anti-inflammatory and lymphocyte activation properties.[10] Users in trials also experienced less radiation induced pain and fewer breaks in treatment. [11]

ECHINACEA ANG There have been no case reports of any drug interactions with Echinacea and "the currently available evidence suggests that echinacea is unlikely to pose serious health threats for patients combining it with conventional drugs."[12] Archaeologists have found evidence that Native Americans may have used Echinacea for more than 400 years to treat infection and wounds. Today uses include a method to shorten the duration of the common cold and flu and reduce symptoms, such as sore throat/pharyngitis, cough, and fever. Several laboratory and animal studies suggest that it contains active substances that enhance the activity of the immune system, relieve pain, reduce inflammation, and have hormonal, antiviral, and antioxidant effects. Often recommended to treat urinary tract infections, vaginal yeast (Candida) infections, ear infections, athlete's foot, sinusitis, hay fever/allergic rhinitis, as well as slow-healing wounds. [13] The constituent base for echinacea is complex, consisting of a wide variety of chemicals of variable effect and potency. Some chemicals may be directly antimicrobial, while others may work at stimulating or modulating different parts of the immune system. Chemical constituents include phenols (cichoric acid and caftaric acid); others that may have important health effects include alkylamides and polysaccharides. The immunomodulatory effects of echinacea preparations are likely caused by fat-soluble alkylamides (alkamides).[14] Alkylamides bind particularly to human CB2 and to a much lesser degree to CB1 receptors; as a result they are implicated in a variety of modulatory functions, including immune suppression, induction of apoptosis, cell migration and inhibition of tumor necrosis factor α TNF-alpha.[15] Although the triggering factors for many autoimmune diseases are not known, one of the key inflammatory mediators in the attending chronic inflammatory process is the cytokine, tumor necrosis factor-alpha (TNF-α). TNF-α overexpression acts as a driver for inflammation that damages cartilage, bone and bowel mucosa, and TNF-α inhibition leads to significant clinical improvements and reduction of this damage. [16]

HYPERICUM has a history of being used as a medicine dating back to ancient Greece with antibacterial and antiviral properties. Its anti-inflammatory properties are useful when applied to the skin to help heal not only wounds and burns, but also eczema and hemorrhoids. In recent years it has been studied extensively as a treatment for depression. A number of studies show that it may help treat mild-to-moderate depression. An early study suggests that it may also help relieve physical and emotional symptoms of Premenstrual syndrome/PMS in some women, including cramps, irritability, food cravings, and breast tenderness. It may also help to improve mood and anxiety during menopause. [17]

THIOSINAMINUM is a trituration of the crystals of allyl sulphocarbamide. Uses include resorb/dissolve/reduction of scar tissue/fibrosis, tumors, strictures, plantar fasciitis, immune system diseases, enlarged glands, eye concerns, scleroderma, tinnitus aurium, amenorrhea, cystic fibrosis, polycystic ovaries, fibroids and pelvic adhesions.[18]

SILVER has a proven record of broad-spectrum antimicrobial activity that includes antibiotic-resistant bacteria, with minimal toxicity toward mammalian cells at low concentrations, and has a less likely tendency than antibiotics to induce resistance due to its activity at multiple bacterial target sites. [19] [20] [21] [22] [23] Silver combined with sulfur is used to topically treat infections of second- and third-degree burns. Wound dressings that contain silver are increasing in importance due to the recent increase of antibiotic-resistant bacteria, such as MRSA.[19]

SULFUR has been in therapeutic use for over 2,000 years, especially for its antiseptic attributes; also helps to control itching/irritation. Sulfur combined with silver is used to topically treat infections of second- and third-degree burns; it also kills a wide variety of bacteria. Also used in the treatment of skin disorders and irritations, such as eczema, dandruff, folliculitis, warts, pityriasis versicolor, psoriasis and acne. It has natural antiseptic properties and plays an essential role in the synthesis of collagen.[24] [25] Well designed studies, most conducted in Israel, suggest that balneotherapy/sulfur can help treat several different kinds of arthritis. People who took sulfur baths and other spa therapies improved strength, had less morning stiffness, had better walking ability, and less inflammation, swelling, and pain in joints, particularly in the neck and back. [26]

URTICA has been used for hundreds of years to treat painful muscles and joints, eczema, arthritis and gout. Today it is also used to treat urinary problems during the early stages of benign prostatic hyperplasia, for urinary tract infections, for hay fever/allergic rhinitis (reduced sneezing and itching), or for treating joint pain, sprains and strains, tendonitis, and insect bites. [27] [28] [29] [30]

CLINICAL STUDIES:

A variety of controlled clinical studies have been favorably performed using one or more of the ingredients herein, but no study has been completed with the combination of all of the AHEALON ingredients.

INDICATIONS:

AHEALON is indicated for the acute and chronic treatment of pain and or inflammation, as well as a general healing aid, an infection deterrent, an agent to help reduce scar tissue and a source of moisturization (dry/cracked/burned skin), that include: all burn injuries, radiation dermatitis, surgical incisions, rashes, pruritic conditions, arthritis/joint pain, lower back pain, wounds, pressure sores, tumors, neuropathic discomfort and any generally painful and or inflamed area. Pain remediation can secondarily benefit sleep quality and duration; pain reduction can also relieve chronic stress induced Cortisol production and thus contribute to less patient stress and anxiety and the reversal of chronic non-healing wounds. Expedited use on pain/trauma patients may quickly control pain such as to reduce the possibility of shock.

CONTRAINDICATIONS:

Although there are no known contraindications, patients who are allergic to any AHEALON ingredient should consult a physician prior to taking the medication. (Refer to Section on Hypersensitivity)

WARNINGS:

Choking Hazard; small parts. Keep out of reach of children.

PRECAUTIONS:

Topical application of AHEALON may cause initial stinging, with progressive desensitization as treatment progresses. Carefully adjust AHEALON dosage to those who might be hypersensitive to any of the ingredients of this drug.

Hypersensitivity: Caution should be used when administering to patients with a history of contact sensitivity to sulfur or silver or to the other ingredients that comprise this drug.

Information for patients: Patients using AHEALON should receive the following information and instructions:

1. AHEALON is to be used throughout the healing process only as directed by your physician.
2. It is important to systematically follow physician advised application times; do not skip AHEALON applications and/or double applications.

Drug Interactions: There are no known AHEALON drug interactions.

Carcinogenesis, mutagenesis, and impairment of fertility: No studies have been done on the carcinogenesis, mutagenesis, or impairment of fertility of AHEALON. In general, at the dilutions herein formulated, homeopathic drugs are not known to cause direct or indirect harm to a fetus. AHEALON should be given to a pregnant woman only if clearly needed.

Effects of each ingredient is not listed as a carcinogen by ACGIH, IARC, NIOSH, NTP, or OSHA; each is a GRAS substance: generally recognized as safe.

Pregnancy Category C. Animal reproduction studies have not been conducted with AHEALON. Pregnant women are given AHEALON only if clearly needed.

Nursing mothers: It is not known whether this drug is secreted in human milk. However, since many drugs are secreted in human milk, caution should be exercised when AHEALON is administered to a nursing woman.

Pediatric use: Carefully adjust AHEALON dosage when treating young children who might have a hypersensitivity to any of the ingredients of this drug.

ADVERSE REACTIONS:

AHEALON contains low doses of active ingredients. Therefore there are minimal known side effects. (see PRECAUTIONS for hypersensitivity information)

OVERDOSAGE:

Due to the low concentrations of active AHEALON ingredients, adverse reactions following overdosage are extremely rare. Care must be taken not to exceed the recommended AHEALON dosage.

DOSAGE AND ADMINISTRATION:

For topical administration (each spray contains approximately 0.15 ML AHEALON) spray 4 to 6 times, 3 to 5 inches away from: all burns, wounds, pressure sores, debrided areas, arthritis, incisions, rashes, scar tissue, painful, bruised and inflamed areas. Use adjunctively with standard measures of care. For intense pain apply every 3 minutes, as pain subsides every 5 minutes, then every 10 minutes, adjusted for each patient, up to hourly. Pain should take longer to return after each application. Generally effective in 12 seconds to 12 minutes; results can last ¼ - 8 hrs. Apply before, during and after debridement; treatment may enhance autolytic debridement. For chronic pain/sores, spray AHEALON as directed, such as every hour, for 2 - 6+ weeks. For maximum absorption, spray should be applied to clean skin/tissue at the beginning of the day and throughout the day per physician directed regimen throughout the healing process – it is important not to miss an application. For burn wounds/grafts, apply to ensure that wounds are kept in a moist condition. AHEALON can be used as a gauze saturant for burns/wounds. Generally use more at first, then use less later. Acting to stop pain/reduce inflammation allows for more tissue perfusion, which allows tissues to acquire more Oxygen and nutrients as vital growth factors for expedited wound closure and healing/infection resistance. Moisturization also helps to ensure a supple wound. AHEALON application to nerve trunk areas, such as neck, could augment effectiveness. Concomitant use with opioid drugs may produce the same analgesic effects with less opioid use. Expedited topical use for trauma/pain patient could act to quickly stop/reduce pain and thus act to reduce the possibility of shock.

Maintenance phase: In order to maintain symptomatic relief, AHEALON should be continued at a physician advised dose level. It is important to use systematically as per physician determined regimen of times and dosage levels throughout the healing period. Treatment duration depends on each individual.

INACTIVE INGREDIENTS:

Sea Minerals, Silver, Water.

HOW SUPPLIED:

Liquid in a 2 ounce/60 ML finger-pump spray bottle made from Cobalt Blue PET for safety; sprayer has a protective over-cap; each bottle contains approximately 400 spray applications at 0.15 ML/spray.
NDC 52793-700-02

REFERENCES:

1. The Homeopathic Pharmacopoeia of the United States (HPUS), December 2000 edition, Falls Church, Virginia.
2. Weremczuk-Jezyna I, Kisiel W, Wysokińska H (2006). "Thymol derivatives from hairy roots of Arnica montana". Plant Cell Rep. 25 (9): 993–6. doi:10.1007/s00299-006-0157-y. PMID 16586074.
3. Ahmad A, et al, Proton translocating ATPase mediated fungicidal activity of eugenol and thymol,Fitoterapia (2010), doi:10.1016/j.fitote.2010.07.020
4. Palaniappan, K. and Holley, R.A. Use of natural antimicrobials to increase antibiotic susceptibility of drug resistant bacteria doi:10.1016/j.ijfoodmicro.2010.04.001.
5. Dorman, H.J.D.; Deans, S.G. Antimicrobial agents from plants: antibacterial activity of plant volatile oils. J. Appl. Microbiol. 2000, 88, 308-316.
6. Ű. Űndeğer a, A. Basaran b, G.H. Degen c, N. Basaran a Antioxidant activities of major thyme ingredients and lack of (oxidative)DNA damage in V79 Chinese hamster lung fibroblast cells at low levels of carvacrol and thymol doi:10.1016/j.fct.2009.05.020
7. Palaniappan, K. and Holley, R.A. Use of natural antimicrobials to increase antibiotic susceptibility of drug resistant bacteria doi:10.1016/j.ijfoodmicro.2010.04.001.
8. The Rural School and Hookworm Disease. Jno A Ferrell, 1914 http://books.google.com/books?id=omYAAAAAYAAJ&dq=THE+RURAL+SCHOOL+AND+hookworm+disease&printsec=frontcover&source=bl&ots=MzB2Qc83MN&sig=XuzEewv27ty90cJ3IxS8fhyh0A4&hl=en&ei=KHKUSsOVKY_QsQOmnNnZBg &sa=X&oi=book_result&ct=result&resnum=1#v=onepage&q=&f=true
9. http://www.umm.edu/altmed/articles/arnica-000222.htm#ixzz1qSojMAmu
10. Jimenez-Medina E, Garcia-Lora A, Paco L et al. (2006). A new extract of the plant Calendula officinalis produces a dual in vitro effect: cytotoxic anti-tumor activity and lymphocyte activation. BMC Cancer. 6:6.
11. Pommier P.et al. J Clinical Oncol 2004; 22:447-1453
12. Izzo AA, Ernst E (2009). "Interactions between herbal medicines and prescribed drugs: an updated systematic review". Drugs 69 (13): 1777–98. doi:10.2165/11317010-000000000-00000. PMID 19719333.
13. http://www.umm.edu/altmed/articles/echinacea-000239.htm#ixzz1qSy3taCX
14. Wichtl Max (Ed.) 2004. Herbal Drugs and Phytopharmaceuticals. medpharm Scientific Publishers/CRC Press. pp 179–186. ISBN 0-8493-1961-7
15. Gertsch Jürg et al. (2004). “Alkylamides from Echinacea are a New Class of Cannabinomimetics”. J. Biol. Chem. 281 (20), pp. 14192–14206. http://www.jbc.org/content/281/20/14192.full.pdf
16. Peter T Nash, MB BS, FRACP, Director, Rheumatology Research Unit, Nambour Hospital, Sunshine Coast1, Timothy H J Florin, MB BS, FRACP, Director of Gastroenterology; and Associate Professor of Medicine, University of Queensland
17. http://www.umm.edu/altmed/articles/st-johns-000276.htm#ixzz1qT3EkJ8B
18. http://www.fertilityproregistry.com/article/remedies-for-obstruction-of-the-epididymis-thiosinaminum-6c.html#ixzz1qYf7JalC
19. Chopra I (April 2007). "The increasing use of silver-based products as antimicrobial agents: a useful development or a cause for concern?". The Journal of Antimicrobial Chemotherapy 59 (4): 587–90. doi:10.1093/jac/dkm006. PMID 17307768.
20. Tian J, Wong KK, Ho CM et al (January 2007). "Topical delivery of silver nanoparticles promotes wound healing". Chemmedchem
  2 (1): 129–36. doi:10.1002/cmdc.200600171. PMID 17075952.
21. Several Silver-Containing Wound Dressings: Abstract and Introduction Medscape.com. 2006-03-23. Retrieved 2010-07-10.
22. Comparison of Two Silver Dressings for Wound Management in Pediatric Burns | WOUNDS". Woundsresearch.com. Retrieved 2010-07-10.
23. Silver Antimicrobial Dressings in Wound Management: A Comparison of Antibacterial, Physical, and Chemical Characteristics ConvaTec Ltd, Flintshire, UK
24. Medical Uses of Sulfur | eHow.com http://www.ehow.com/info_8680883_medicaluses-sulfur.html#ixzz1qr0aX1qZ
25. http://www.umm.edu/altmed/articles/sulfur-000328.htm#ixzz1qr306aDH
26. http://www.umm.edu/altmed/articles/sulfur-000328.htm#ixzz1qr49WWIc
27. Chrubasik JE, Roufogalis BD, Wagner H, Chrubasik S. A comprehensive review on the stinging nettle effect and efficacy profiles. Part II: urticae radix. Phytomedicine. 2007;14(7-8):568-79.
28. Ernst E, Chrubasik S. Phyto-anti-inflammatories. A systematic review of randomized, placebo-controlled, double-blind trials. Rheum Dis Clin North Am. 2000;26(1):13-27.
29. Helms S, Miller A. Natural treatment of chronic rhinosinusitis. Altern Med Rev. 2006 Sept;11(3):196-207.
30. http://www.umm.edu/altmed/articles/stinging-nettle-000275.htm#ixzz1qYJeFKiG

Princeton BIOTECHNOLOGY
Innovations for Health and Healing™

Princeton Biotechnology Corporation, Barrington, NJ 08007 USA
www.ahealon.com 800-250-9006

Revised November 2012

PACKAGE LABEL

PRESCRIPTION ONLY MEDICINE
STOPS PAIN
in 12 sec – 12 min
Ahealon®
6-in-1 TOPICAL SPRAY
for pain, burns, inflammation, wounds, arthritis, incisions
Stops Pain
Moisturizes
Aids Healing
Fights Infection
Reduces Scar Tissue
Reduces Inflammation
use often throughout the healing process
2 oz / 60 ml
Distributed By:
Princeton Biotechnology Corporation
FDA NDC 52793-700-02
Stops Pain 12 sec – 12 min
Burns, Wounds, Arthritis
Ahealon®
Directions: Spray 4 to 6 times, 3 to 5 inches away from: all burns, wounds, pressure sores, arthritis, incisions, painful and inflamed areas.
Reapply as needed for pain. Pain takes longer to return after an application. Use adjunctively with standard measures of care.
Generally Effective in 12 sec to 12 min; can last ¼ - 8 hrs. For chronic pain spray as your doctor directs for 2 - 6+ weeks.
Helps: stop pain, reduce inflammation (allows more tissue perfusion = more Oxygen and nutrients as vital growth factors for wound closure and healing/infection resistance), fight infection, stop scar tissue; also for moisturization.
Important to Spray Often: such as every ½ hr; as healing progresses ≥ 8 times per day throughout the healing process.
All Rights Reserved, 2012©Princeton Biotechnology Corporation
Safety: Nontoxic, opiate free, non-addictive, may sting initially, scent free, eye safe, steroid free, non-staining, non-greasy, taste free, hypoallergenic (see insert).
Warning: Choking Hazard-Small Parts (spray is child safe)
Keep out of reach of children.
If pregnant or nursing ask your health professional before use.
Active Ingredients: HPUS: Arnica 10C/30C/50M, Calendula 10C/30C/50M, Echinacea ANG 10C/30C/50M, Hypericum 10C/30C/50M, Silver 10C/30C/50M, Sulfur 10C/30C/50M, Thiosinaminum 10C/30C/50M, Urtica 10C/30C/50M.
Other Ingredients: Water, Sea Minerals, Silver.
Made in USA
U. S. Patent Pending
Manufactured for:
Princeton Biotechnology Corporation,
Barrington, NJ 08007 USA
800-250-9006 Ahealon.com
Princeton BIOTECHNOLOGY™
Innovations for Health and Healing™